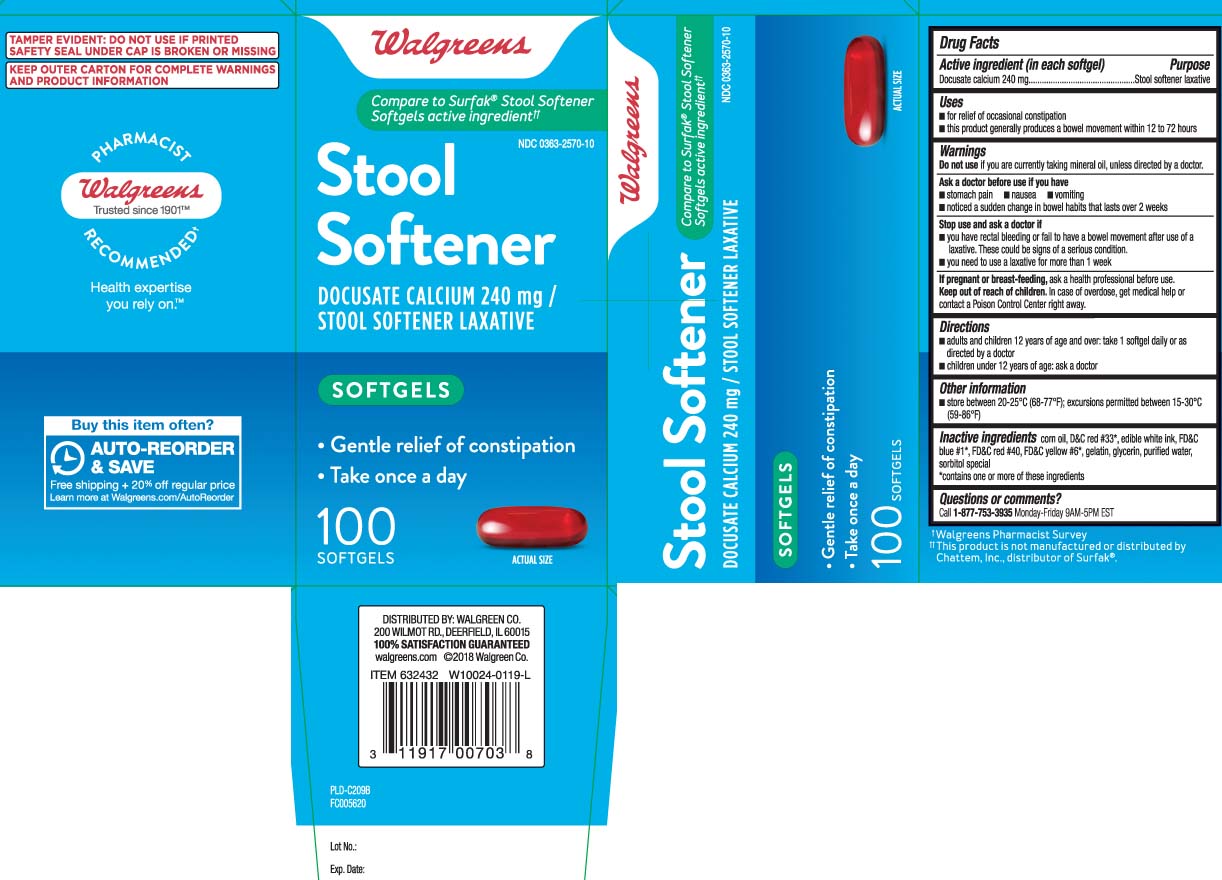 DRUG LABEL: Stool Softener
NDC: 0363-2570 | Form: CAPSULE, LIQUID FILLED
Manufacturer: Walgreens
Category: otc | Type: HUMAN OTC DRUG LABEL
Date: 20240710

ACTIVE INGREDIENTS: DOCUSATE CALCIUM 240 mg/1 1
INACTIVE INGREDIENTS: CORN OIL; D&C RED NO. 33; FD&C RED NO. 40; GELATIN; GLYCERIN; WATER; SORBITOL; FD&C BLUE NO. 1; FD&C YELLOW NO. 6; SORBITAN

Drug Facts

Active ingredient (in each softgel)

Docusate Calcium 240 mg

Purpose

Stool softener laxative

Uses

- for relief of occasional constipation
- this product generally produces a bowel movement within 12 to 72 hours

Warnings

Do not use

if you are currently taking mineral oil, unless directed by a doctor.

Ask a doctor before use if you have

- stomach pain
- nausea
- vomiting
- noticed a sudden change in bowel habits that lasts over 2 weeks

Stop use and ask a doctor if

- you have rectal bleeding or fail to have a bowel movement after use of a laxative. These could be signs of a serious condition.
- you need to use a laxative for more than 1 week

If pregnant or breast-feeding,

ask a health care professional before use.

Keep out of reach of children.

In case of overdose, get medical help or contact a Poison Control Center right away.

Directions

- adults and children 12 years of age and over: take 1 softgel daily or as directed by a doctor
- children under 12 years of age: ask a doctor

Other information

- store at 20-25ºC (68º-77ºF); excursions permitted between 15-30ºC (59-86ºF)

Inactive ingredients

corn oil, D&C red #33*, edible white ink, FD&C blue #1*, FD&C red #40, FD&C yellow #6*, gelatin, glycerin, purified water, sorbitol special

*contains one or more of these ingredients

Questions or comments?

Call 1-877-753-3935 Monday-Friday 9AM-5PM EST

Principal Display Panel

Compare to Surfak® Stool Softener Softgels active ingredient††

Stool Softener

DOCUSATE CALCIUM 240 mg /

STOOL SOFTENER LAXATIVE

SOFTGELS

- Gentle relief of constipation
- Take once a day

SOFTGELS

††This product is not manufactured or distributed by Chattem Inc., distributor of Surfak®.

TAMPER EVIDENT: DO NOT USE IF PRINTED SAFETY SEAL UNDER CAP IS BROKEN OR MISSING

KEEP OUTER CARTON FOR COMPLETE WARNINGS AND PRODUCT INFORMATION

DISTRIBUTED BY: WALGREEN CO.

200 WILMOT RD., DEERFIELD, IL 60015

walgreens.com

Product Label

WALGREENS Stool Softener